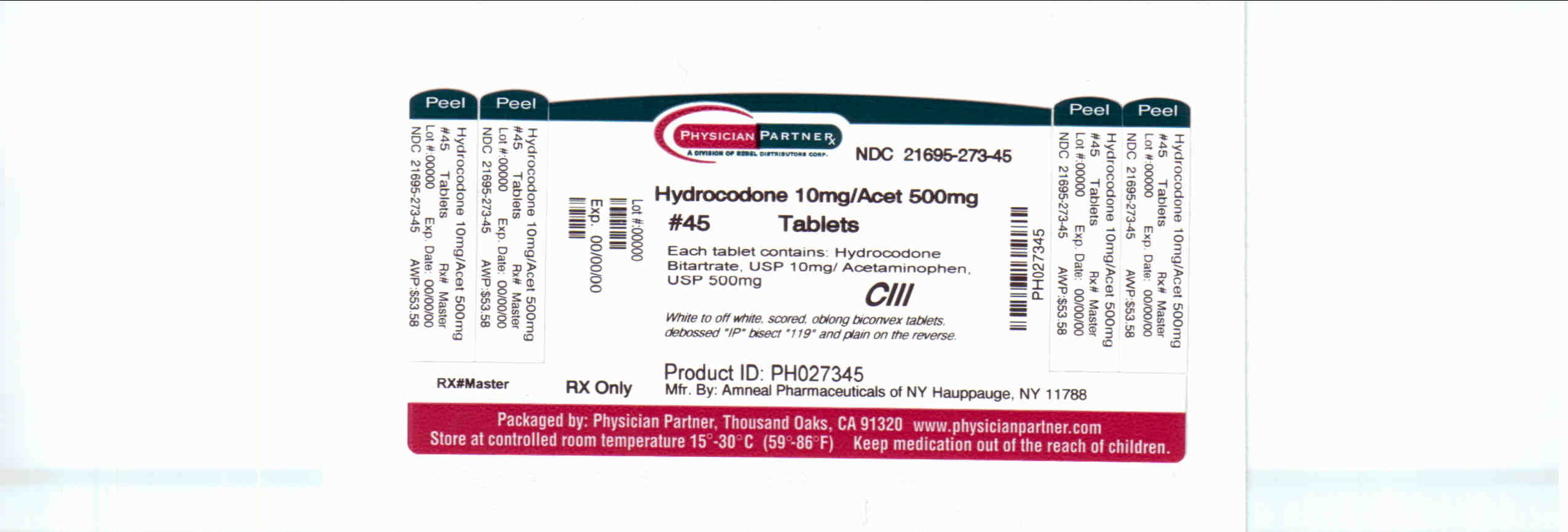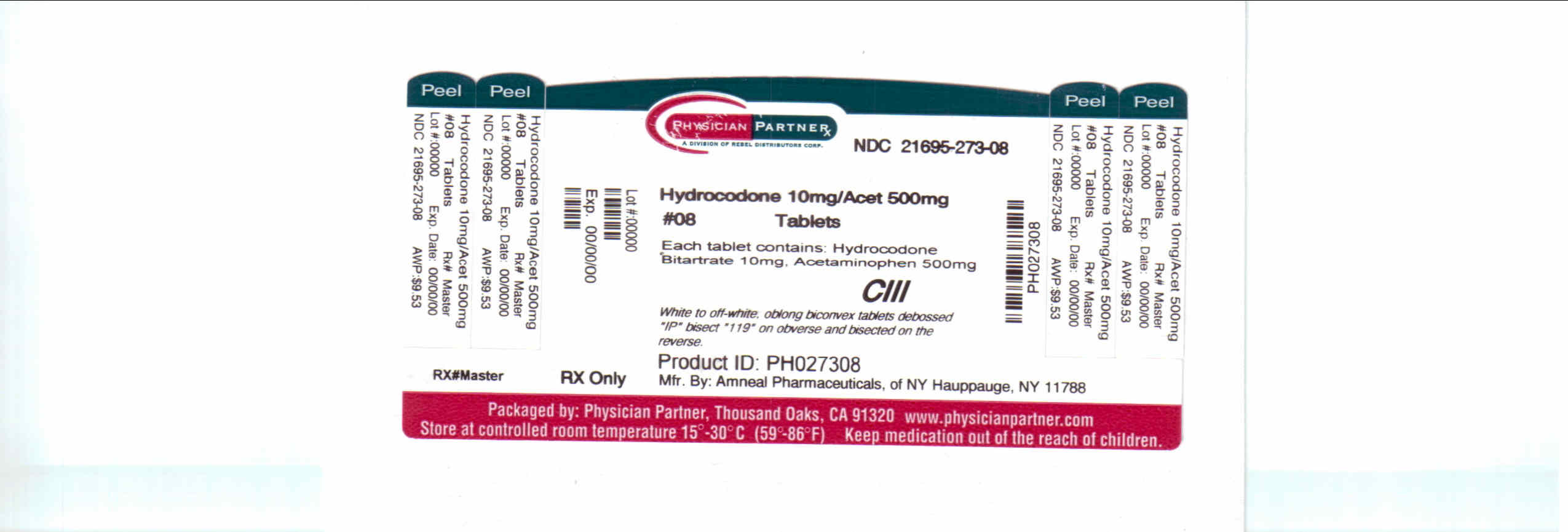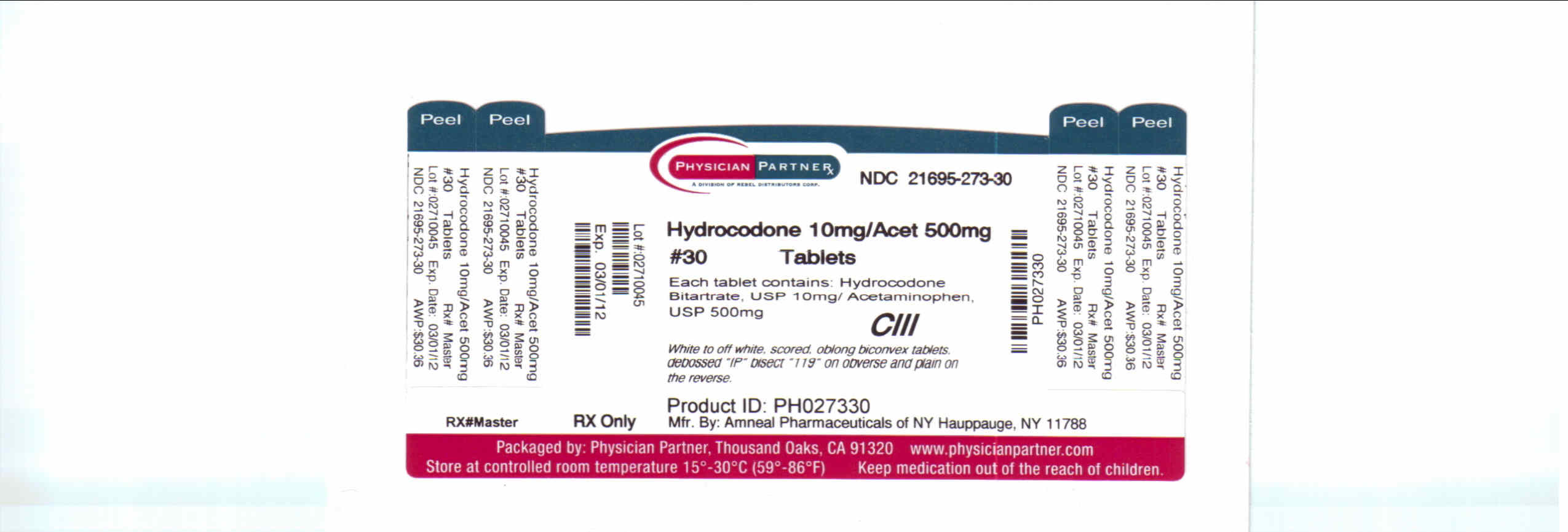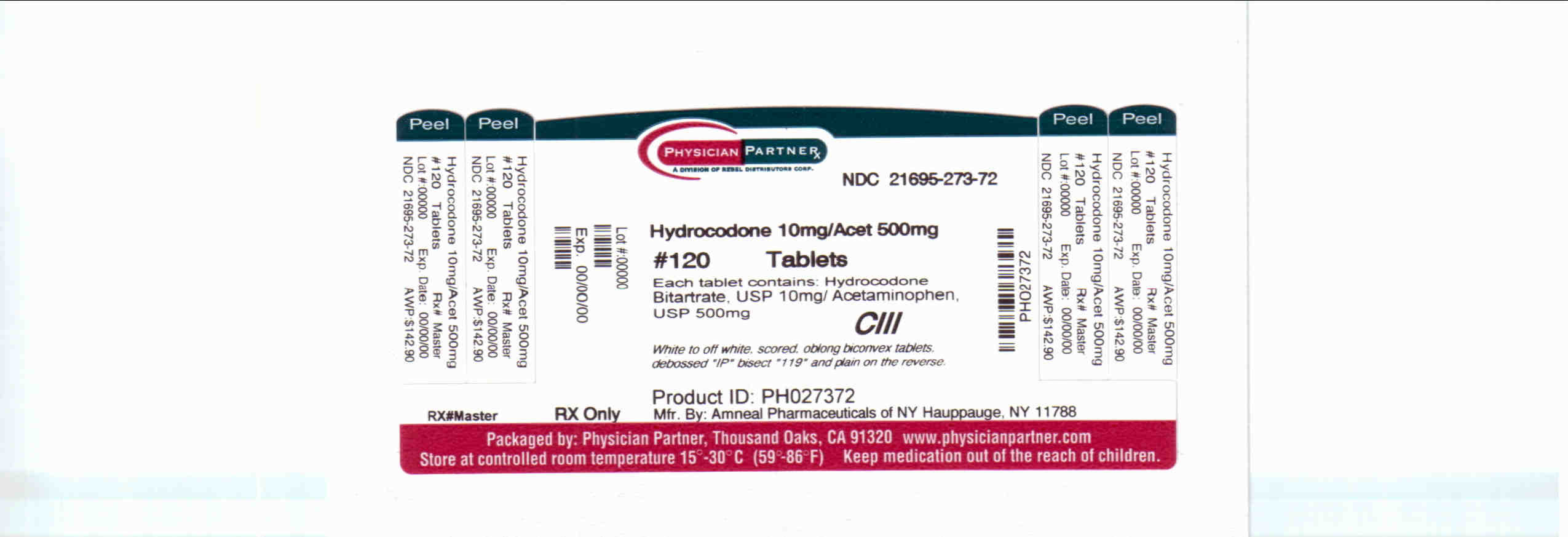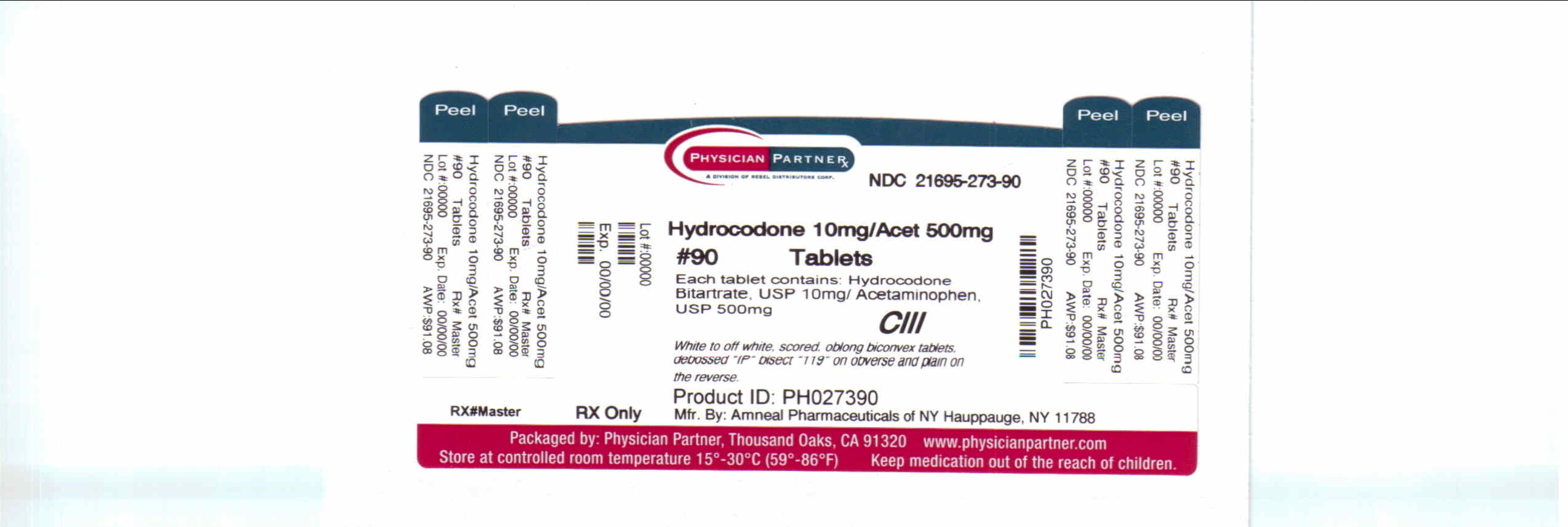 DRUG LABEL: Hydrocodone Bitartrate and Acetaminophen
NDC: 21695-273 | Form: TABLET
Manufacturer: Rebel Distributors Corp
Category: prescription | Type: HUMAN PRESCRIPTION DRUG LABEL
Date: 20101228
DEA Schedule: CIII

ACTIVE INGREDIENTS: HYDROCODONE BITARTRATE 10 mg/1 1; ACETAMINOPHEN 500 mg/1 1
INACTIVE INGREDIENTS: HYDRATED SILICA; CROSCARMELLOSE SODIUM; CROSPOVIDONE; D&C RED NO. 27; D&C RED NO. 30; MAGNESIUM STEARATE; CELLULOSE, MICROCRYSTALLINE; COPOVIDONE; STARCH, CORN; STEARIC ACID

Hydrocone Bitartrate and Acetaminophen

DESCRIPTION

DESCRIPTIONHydrocodone bitartrate and acetaminophen is supplied in tablet form for oral administration.Hydrocodone bitartrate is an opioid analgesic and antitussive and occurs as fine, white crystals or as a crystalline powder. It is affectedby light. The chemical name is 4,5a-Epoxy-3-methoxy-17-methylmorphinan-6-one tartrate (1:1) hydrate (2:5). It has the followingstructural formula: Acetaminophen, 4-hydroxyacetanilide, a slightly bitter, white, odorless, crystalline powder, is a non-opiate, non-salicylate analgesicand antipyretic. It has the following structural formula: Hydrocodone Bitartrate and Acetaminophen Tablets USP for oral administration are available in a variety of strengths as described inthe following table. Hydrocodone Strength Bitartrate Acetaminophen 2.5 mg/500mg 2.5 mg 500 mg 5 mg/500 mg 5 mg 500 mg 7.5 mg/325 mg 7.5 mg 325 mg 7.5 mg/500 mg 7.5 mg 500 mg 7.5 mg/650 mg 7.5 mg 650 mg 7.5 mg/750 mg 7.5 mg 750 mg 10 mg/325 mg 10 mg 325 mg 10 mg/500 mg 10 mg 500 mg 10 mg/650 mg 10 mg 650 mg 10 mg/660 mg 10 mg 660 mg 10 mg/750 mg 10 mg 750 mg In addition, each tablet contains the following

INACTIVE INGREDIENT

inactive ingredients: anhydrous lactose, croscarmellose sodium, crospovidone,magnesium stearate, microcrystalline cellulose, povidone, starch and stearic acid; except the 7.5 mg/325 mg, 10 mg/325 mg and 10 page 2 of 7 mg/500 mg tablets do not contain anhydrous lactose. The 7.5 mg/325 mg tablets include FD&C Yellow #6 Aluminum Lake; the 7.5mg/650 mg tablets include FD&C Red #40 Aluminum Lake; the 10 mg/325 mg and 10 mg/750 mg tablets include D&C Yellow #10Aluminum Lake; the 10 mg/500 mg tablets include FD&C Blue #2 Aluminum Lake; and the 10 mg/650 mg tablets include FD&CBlue #1 Aluminum Lake and D&C Yellow #10 Aluminum Lake. Meets USP Dissolution Test 1.

CLINICAL PHARMACOLOGY

CLINICAL PHARMACOLOGYHydrocodone is a semisynthetic narcotic analgesic and antitussive with multiple actions qualitatively similar to those of codeine. Mostof these involve the central nervous system and smooth muscle. The precise

mechanism of action of hydrocodone and other opiates isnot known, although it is believed to relate to the existence of opiate receptors in the central nervous system. In addition to analgesia,narcotics may produce drowsiness, changes in mood and mental clouding.The analgesic action of acetaminophen involves peripheral influences, but the specific mechanism is as yet undetermined. Antipyreticactivity is mediated through hypothalamic heat regulating centers. Acetaminophen inhibits prostaglandin synthetase. Therapeuticdoses of acetaminophen have negligible effects on the cardiovascular or respiratory systems; however, toxic doses may causecirculatory failure and rapid, shallow breathing.

PHARMACOKINETICS

Pharmacokinetics:The behavior of the individual components is described below.Hydrocodone: Following a 10 mg oral dose of hydrocodone administered to five adult male subjects, the mean peak concentration was 23.6 261 5.2ng/mL. Maximum serum levels were achieved at 1.3 261 0.3 hours and the half-life was determined to be 3.8 261 0.3 hours. Hydrocodoneexhibits a complex pattern of metabolism including O-demethylation, N-demethylation and 6-ketoreduction to the corresponding 6-aand 6-337 -hydroxymetabolites. See

OVERDOSAGE

OVERDOSAGE for toxicity information.Acetaminophen: Acetaminophen is rapidly absorbed from the gastrointestinal tract and is distributed throughout most body tissues. The plasma half-lifeis 1.25 to 3 hours, but may be increased by liver damage and following overdosage. Elimination of acetaminophen is principally byliver metabolism (conjugation) and subsequent renal excretion of metabolites. Approximately 85% of an oral dose appears in the urinewithin 24 hours of administration, most as the glucuronide conjugate, with small amounts of other conjugates and unchanged drug.See OVERDOSAGE for toxicity information.INDICATIONS AND USAGEHydrocodone and acetaminophen tablets are indicated for the relief of moderate to moderately severe pain.

CONTRAINDICATIONS

CONTRAINDICATIONSThis product should not be administered to patients who have previously exhibited Hypersensitivity to hydrocodone oracetaminophen.Patients known to be hypersensitive to other opioids may exhibit cross-sensitivity to hydrocodone.

WARNINGS

WARNINGSRespiratory Depression:At high doses or in sensitive patients, hydrocodone may produce dose-related respiratory depression by acting directly on the brainstem respiratory center. Hydrocodone also affects the center that controls respiratory rhythm, and may produce irregular and periodicbreathing.Head Injury and Increased Intracranial Pressure:The respiratory depressant effects of narcotics and their capacity to elevate cerebrospinal fluid pressure may be markedly exaggeratedin the presence of head injury, other intracranial lesions or a pre-existing increase in intracranial pressure. Furthermore, narcoticsproduce

ADVERSE REACTIONS

adverse reactions which may obscure the clinical course of patients with head injuries.Acute Abdominal Conditions:The administration of narcotics may obscure the diagnosis or clinical course of patients with acute abdominal conditions.

PRECAUTIONS

PRECAUTIONSGeneralSpecial Risk Patients: As with any narcotic analgesic agent, hydrocodone bitartrate and acetaminophen tablets should be used withcaution in elderly or debilitated patients, and those with severe impairment of hepatic or renal function, hypothyroidism, Addison222sdisease, prostatic hypertrophy or urethal stricture. The usual precautions should be observed and the possibility of respiratorydepression should be kept in mind.Cough Reflex : Hydrocodone suppresses the cough reflex; as with all narcotics, caution should be exercised when hydrocodonebitartrate and acetaminophen tablets are used postoperatively and in patients with pulmonary disease. page 3 of 7

INFORMATION FOR PATIENTS

Information for PatientsHydrocodone, like all narcotics, may impair the mental and/or physical abilities required for the performance of potentially hazardoustasks such as driving a car or operating machinery; patients should be cautioned accordingly.Alcohol and other CNS depressants may produce an additive CNS depression, when taken with this combination product, and shouldbe avoided.Hydrocodone may be habit forming. Patients should take the drug only for as long as it is prescribed, in the amounts prescribed, andno more frequently than prescribed.Hydrocodone suppresses the cough reflex; as with all narcotics, caution should be exercised when hydrocodone bitartrate andacetaminophen tablets are used postoperatively and in patients with pulmonary disease.

LABORATORY TESTS

Laboratory TestsIn patients with severe hepatic or renal disease, effects of therapy should be monitored with serial liver and/or renal function tests.

DRUG INTERACTIONS

Drug interactionsPatients receiving other narcotic analgesics, antihistamines, antipsychotics, antianxiety agents, or other CNS depressants (includingalcohol) concomitantly with hydrocodone bitartrate and acetaminophen tablets may exhibit an additive CNS depression. Whencombined therapy is contemplated, the dose of one or both agents should be reduced.The use of MAO inhibitors or tricyclic antidepressants with hydrocodone preparations may increase the effect of either theantidepressant or hydrocodone.Drug/Laboratory Test InteractionsAcetaminophen may produce false-positive test results for urinary 5-hydroxyindoleacetic acid.Carcinogenesis, Mutagenesis, Impairment of FertilityNo adequate studies have been conducted in animals to determine whether hydrocodone or acetaminophen have a potential forcarcinogenesis, mutagenesis, or impairment of fertility.

PREGNANCY

TERATOGENIC EFFECTS

Teratogenic effectsPregnancy Category C:There are no adequate and well-controlled studies in pregnant women. Hydrocodone bitartrate and acetaminophen tablets should beused during pregnancy only if the potential benefit justifies the potential risk to the fetus.

NONTERATOGENIC EFFECTS

Nonteratogenic effectsBabies born to mothers who have been taking opioids regularly prior to delivery will be physically dependent. The withdrawal signsinclude irritability and excessive crying, tremors, hyperactive reflexes, increased respiratory rate, increased stools, sneezing, yawning,vomiting, and fever. The intensity of the syndrome does not always correlate with the duration of maternal opioid use or dose. There isno consensus on the best method of managing withdrawal.Labor and DeliveryAs with all narcotics, administration of this product to the mother shortly before delivery may result in some degree of respiratorydepression in the newborn, especially if higher doses are used.

NURSING MOTHERS

Nursing MothersAcetaminophen is excreted in breast milk in small amounts, but the significance of its effects on nursing infants is not known. It is notknown whether hydrocodone is excreted in human milk. Because many drugs are excreted in human milk and because of thepotential for serious adverse reactions in nursing infants from hydrocodone and acetaminophen, a decision should be made whether todiscontinue nursing or to discontinue the drug, taking into account the importance of the drug to the mother.

PEDIATRIC USE

Pediatric UseSafety and effectiveness in pediatric patients have not been established.

GERIATRIC USE

CLINICAL STUDIES

Clinical studies of hydrocodone bitartrate 5 mg and acetaminophen 500 mg did not include sufficient numbers of subjects aged 65and over to determine whether they respond differently from younger subjects. Other reported clinical experience has not identifieddifferences in responses between the elderly and younger patients. In general, dose selection for an elderly patient should be cautious,usually starting at the low end of the dosing range, reflecting the greater frequency of decreased hepatic, renal, or cardiac function, andof concomitant disease or other drug therapy.Hydrocodone and the major metabolites of acetaminophen are known to be substantially excreted by the kidney. Thus the risk of toxicreactions may be greater in patients with impaired renal function due to the accumulation of the parent compound and/or metabolites page 4 of 7 in the plasma. Because elderly patients are more likely to have decreased renal function, care should be taken in dose selection, and itmay be useful to monitor renal function.Hydrocodone may cause confusion and over-sedation in the elderly; elderly patients generally should be started on low doses ofhydrocodone bitartrate and acetaminophen tablets and observed closely.ADVERSE REACTIONSThe most frequently reported adverse reactions are lightheadedness, dizziness, sedation, nausea and vomiting. These effects seem tobe more prominent in ambulatory than in nonambulatory patients, and some of these adverse reactions may be alleviated if the patientlies down.Other adverse reactions include:Central Nervous System: Drowsiness, mental clouding, lethargy, impairment of mental and physical performance, anxiety, fear,dysphoria, psychic

DEPENDENCE

dependence, mood changes.Gastrointestinal System: Prolonged administration of hydrocodone bitartrate and acetaminophen tablets may produce constipation.Genitourinary System: Ureteral spasm, spasm of vesical sphincters and urinary retention have been reported with opiates.Respiratory Depression: Hydrocodone bitartrate may produce dose-related respiratory depression by acting directly on the brainstem respiratory centers (see OVERDOSAGE).Special Senses: Cases of hearing impairment or permanent loss have been reported predominantly in patients with chronic overdose.Dermatological: Skin rash, pruritus.The following adverse drug events may be borne in mind as potential effects of acetaminophen: allergic reactions, rash,thrombocytopenia, agranulocytosis.Potential effects of high dosage are listed in the OVERDOSAGE section.

DRUG ABUSE AND DEPENDENCE

DRUG

ABUSE

ABUSE AND DEPENDENCE

CONTROLLED SUBSTANCE

Controlled SubstanceHydrocodone bitartrate and Acetaminophen Tablets are classified as a Schedule lll controlled substance.Abuse and DependencePsychic dependence, physical dependence, and tolerance may develop upon repeated administration of narcotics; therefore, thisproduct should be prescribed and administered with caution. However, psychic dependence is unlikely to develop when hydrocodonebitartrate and acetaminophen tablets are used for a short time for the treatment of pain.Physical dependence, the condition in which continued administration of the drug is required to prevent the appearance of awithdrawal syndrome, assumes clinically significant proportions only after several weeks of continued narcotic use, although somemild degree of physical dependence may develop after a few days of narcotic therapy. Tolerance, in which increasingly large dosesare required in order to produce the same degree of analgesia, is manifested initially by a shortened duration of analgesic effect, andsubsequently by decreases in the intensity of analgesia. The rate of development of tolerance varies among patients.OVERDOSAGEFollowing an acute overdosage, toxicity may result from hydrocodone or acetaminophen.Signs and Symptoms:Hydrocodone: Serious overdose with hydrocodone is characterized by respiratory depression (a decrease in respiratory rate and/or tidal volume,Cheyne-Stokes respiration, cyanosis), extreme somnolence progressing to stupor or coma, skeletal muscle flaccidity, cold and clammyskin, and sometimes bradycardia and hypotension. In severe overdosage, apnea, circulatory collapse, cardiac arrest and death mayoccur.Acetaminophen: In acetaminophen overdosage: dose-dependent, potentially fatal hepatic necrosis is the most serious adverse effect. Renal tubularnecrosis, hypoglycemic coma, and thrombocytopenia may also occur.Early symptoms following a potentially hepatotoxic overdose may include: nausea, vomiting, diaphoresis and general malaise.Clinical and laboratory evidence of hepatic toxicity may not be apparent until 48 to 72 hours post-ingestion.In adults, hepatic toxicity has rarely been reported with acute overdoses of less than 10 grams, or fatalities with less than 15 grams.Treatment:A single or multiple overdose with hydrocodone and acetaminophen is a potentially lethal polydrug overdose, and consultation with aregional poison control center is recommended.Immediate treatment includes support of cardiorespiratory function and measures to reduce drug absorption. Vomiting should beinduced mechanically, or with syrup of ipecac, if the patient is alert (adequate pharyngeal and laryngeal reflexes). Oral activatedcharcoal (1 g/kg) should follow gastric emptying. The first dose should be accompanied by an appropriate cathartic. If repeated dosesare used, the cathartic might be included with alternate doses as required. Hypotension is usually hypovolemic and should respond to page 5 of 7 fluids. Vasopressors and other supportive measures should be employed as indicated. A cuffed endotracheal tube should be insertedbefore gastric lavage of the unconscious patient and, when necessary, to provide assisted respiration.Meticulous attention should be given to maintaining adequate pulmonary ventilation. In severe cases of intoxication, peritonealdialysis, or preferably hemodialysis may be considered. If hypoprothrombinemia occurs due to acetaminophen overdose, vitamin Kshould be administered intravenously.Naloxone, a narcotic antagonist, can reverse respiratory depression and coma associated with opioid overdose. Naloxonehydrochloride 0.4 mg to 2 mg is given parenterally. Since the duration of action of hydrocodone may exceed that of the naloxone,the patient should be kept under continuous surveillance and repeated doses of the antagonist should be administered as needed tomaintain adequate respiration. A narcotic antagonist should not be administered in the absence of clinically significant respiratory orcardiovascular depression.If the dose of acetaminophen may have exceeded 140 mg/kg, acetylcysteine should be administered as early as possible. Serumacetaminophen levels should be obtained, since levels four or more hours following ingestion help predict acetaminophen toxicity. Donot await acetaminophen assay results before initiating treatment. Hepatic enzymes should be obtained initially, and repeated at 24-hour intervals.Methemoglobinemia over 30% should be treated with methylene blue by slow intravenous administration.The toxic dose for adults for acetaminophen is 10 g.DOSAGE AND ADMINISTRATIONDosage should be adjusted according to the severity of the pain and the response of the patient. However, it should be kept in mindthat tolerance to hydrocodone can develop with continued use and that the incidence of untoward effects is dose related. 2.5 mg/500 mg5 mg/500 mg The usual adult dosage is one or two tablets every four to six hours as needed for pain. The totaldaily dosage should not exceed 8 tablets 7.5 mg/325 mg7.5 mg/500 mg7.5 mg/650 mg The usual adult dosage is one tablet every four to six hours as needed for pain. The total dailydosage should not exceed 6 tablets. 7.5 mg/750 mg The usual adult dosage is one tablet every four to six hours as needed for pain. The total dailydosage should not exceed 5 tablets. 10 mg/325 mg10 mg/500 mg10 mg/650 mg10 mg/660 mg The usual adult dosage is one tablet every four to six hours as needed for pain. The total dailydosage should not exceed 6 tablets. 10 mg/750 mg The usual adult dosage is one tablet every four to six hours as needed for pain. The total dailydosage should not exceed 5 tablets.

HOW SUPPLIED

HOW SUPPLIEDHydrocodone Bitartrate and Acetaminophen Tablets USP are available in10 mg/500 mg 10 mg hydrocodone bitartrate and 500 mg acetaminophen, capsule-shaped, blue tablets bisected on one side anddebossed with WATSON 540 on the other side, supplied in unit dose packages of :

120 NDC 21695-273-72

90 NDC 21695-273-90

60 NDC 21695-273-60

45 NDC 21695-273-45

30 NDC 21695-273-30

28 NDC 21695-273-28

12 NDC 21695-273-12

8 NDC 21695-273-08

Store at 20260-25260C (68260-77260F). [See USP controlled room temperature].Rx onlyManufactured by:Watson Laboratories, Inc.Corona, CA 92880 USADistributed by:Watson Pharma, Inc.Corona, CA 92880 USA

Repackaged by:

Rebel Distributors Corp

Thousand Oaks, CA 91320